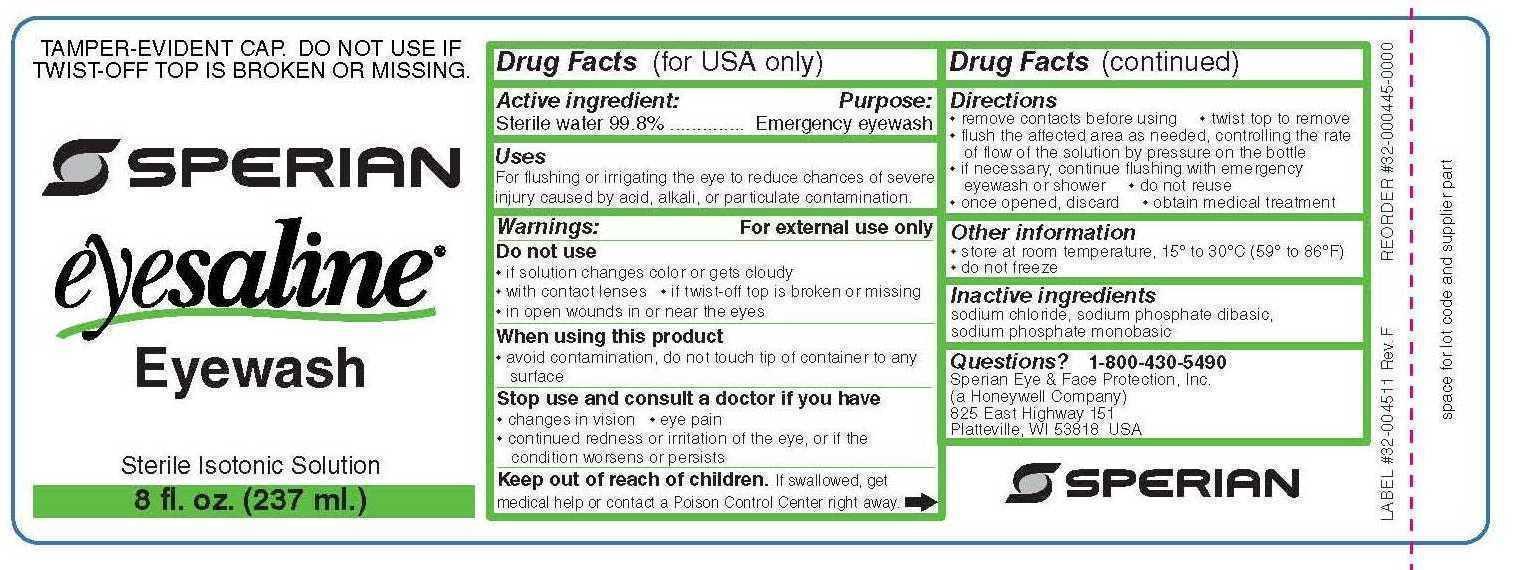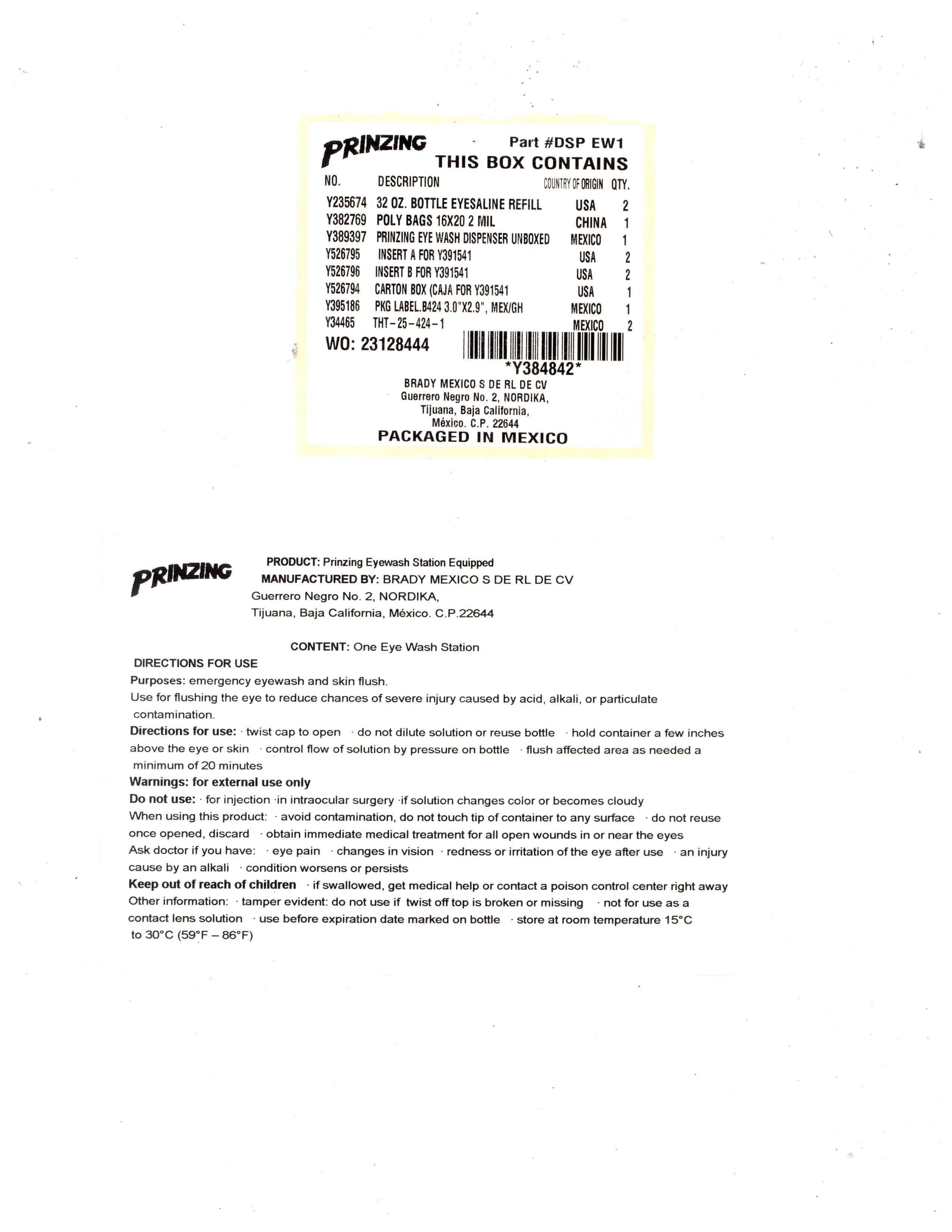 DRUG LABEL: Prinzing Eye Wash Station
NDC: 55925-100 | Form: KIT | Route: OPHTHALMIC
Manufacturer: BRADY MEXICO, S. DE R.L. DE C.V.
Category: other | Type: MEDICAL DEVICE
Date: 20140624

ACTIVE INGREDIENTS: WATER 99.8 mL/100 mL
INACTIVE INGREDIENTS: SODIUM CHLORIDE; SODIUM PHOSPHATE, MONOBASIC, MONOHYDRATE; SODIUM PHOSPHATE, DIBASIC ANHYDROUS

Prinzing Eyewash Station

PACKAGE LABEL

PRINZING Part #DSP EW1

PRINZING

Part #DSP EW1

THIS BOX CONTAINS

NO. DESCRIPTION COUNTRY OF ORIGIN QTY.

Y235674 32 OZ. BOTTLE EYESALINE REFILL USA 2

Y382769 POLY BAGS 16X20 2 MIL CHINA 1

Y389397 PRINZING EYE WASH DISPENSER UNBOXED MEXICO 1

Y526795 INSERT A FOR Y391541 USA 2

Y526796 INSERT B FOR Y391541 USA 2

Y526794 CARTON BOX (CAJA) FOR Y391541 USA 1

Y395186 PKG LABEL .B424 3.0"X2.9", MEX/GH MEXICO 1

Y34465 THT-25-424-1 MEXICO 2

WO: 23128444

*Y384842*

BRADY MEXICO S DE RL DE CV

Guerrero Negro No. 2, NORDIKA,

Tijuana, Baja California,

Mexico, C.P. 22644

PACKAGED IN MEXICO

PRINZING

PRODUCT: Prinzing Eyewash Station Equipped

MANUFACTURED BY: BRADY MEXICO S DE RL DE CV

Guerrero Negro No. 2, NORDIKA,

Tijuana, Baja California, Mexico, C.P. 22644

CONTENT: One Eye Wash Station

DIRECTIONS FOR USE

Purposes: emergency eyewash and skin flush.

Use for flushing the eye to reduce chances of severe injury caused by acid, alkali, or particulate contamination.

Directions for use: - twist cap open - do not dilute solution or reuse bottle - hold container a few inches above the eye or skin - control flow of solution by pressure on bottle - flush affected area as needed a minimum of 20 minutes

Warnings: for external use only

Do not use: - for injection - intraocular surgery - if solution changes color or becomes cloudy

When using this product: - avoid contamination, do not touch tip of container to any surface - do not reuse - once opened, discard - obtain immediate medical treatment for all open wounds in or near the eyes

Ask doctor if you have: - eye pain - changes in vision - redness or irritation of the eye after use - an injury cause by alkali - condition worsens or persists

Keep out of reach of children - If swallowed, get medical help or contact a poision control center right away

Other information: - tamper evident: do not use if twist off top is broken or missing - not for use as a contact lens solution - use before expiration date marked on bottle - store at room temperature 15 degrees Celcius to 30 degrees Celcius (59 degrees - 86 degrees Fahrenheit)

Active Ingredient:

Sterile water 99.8%

Purpose:

Emergency eyewash

Uses

For flushing or irrigating the eye to reduce chances of severe injury caused by acid, alkali, or particulate contamination.

Warnings: For external use only

Do not use

- if solution changes color or gets cloudy
- with contact lenses
- if twist-off top is broken or missing
- in open wounds in or near the eyes

When using this product

- avoid contamination, do not touch tip of container to any surface

Stop use and consult a doctor if you have

- changes in vision
- eye pain
- continued redness or irritation of the eye, or if the condition worsens or persists

Keep out of reach of children. If swallowed, get medical help or contact a Poison Control Center right away.

Directions

- remove contacts before using
- twist top to remove
- flush the affected area as needed, controlling the rate of flow of the solution by pressure on the bottle
- if necessary, continue flushing with emergency eyewash or shower
- do not reuse
- once opened, discard
- obtain medical treatment

Other information

- store at room temperature, 15 degrees to 30 degrees Celsius (59 degrees to 86 degrees Fahrenheit)
- do not freeze

Inactive ingredients

sodium chloride, sodium phosphate dibasic, sodium phosphate monobasic

Questions?1-800-430-5490

Sperian Eye & Face Protection, Inc.

(a Honeywell Company)

825 East Highway 151

Platteville, WI 53818 USA

PACKAGE LABEL

TAMPER-EVIDENT CAP. DO NOT USE IF TWIST-OFF TOP IS BROKEN OR MISSING

SPERIAN

eyesaline

Eyewash

Sterile Isotonic Solution

32 fl. oz. (946 ml.)